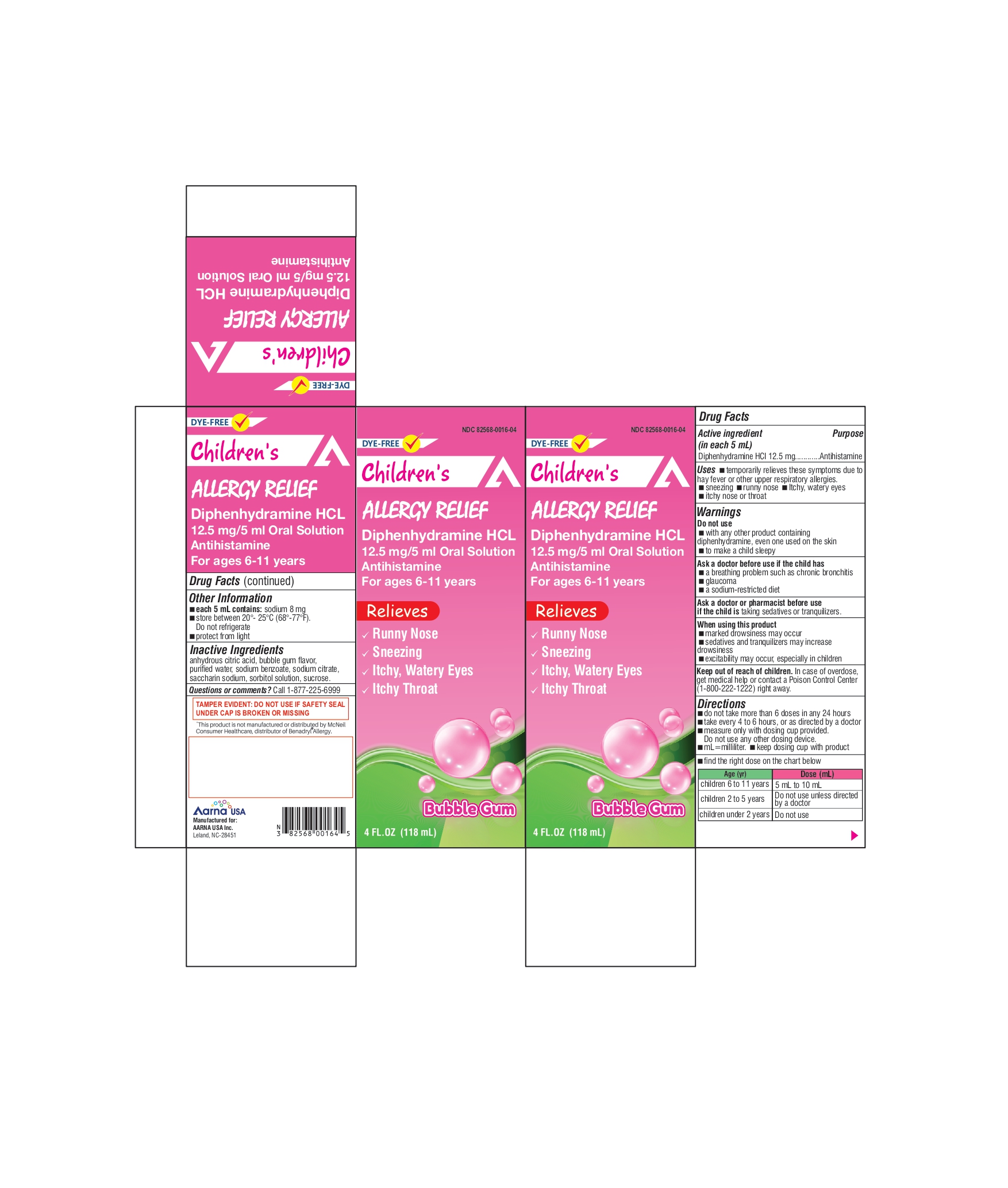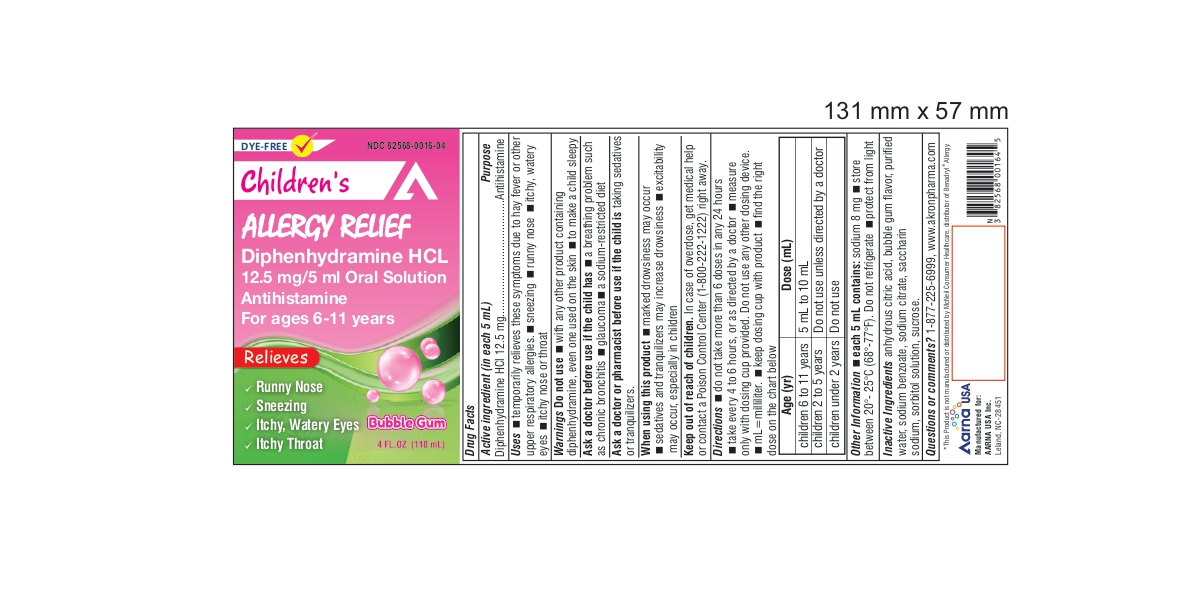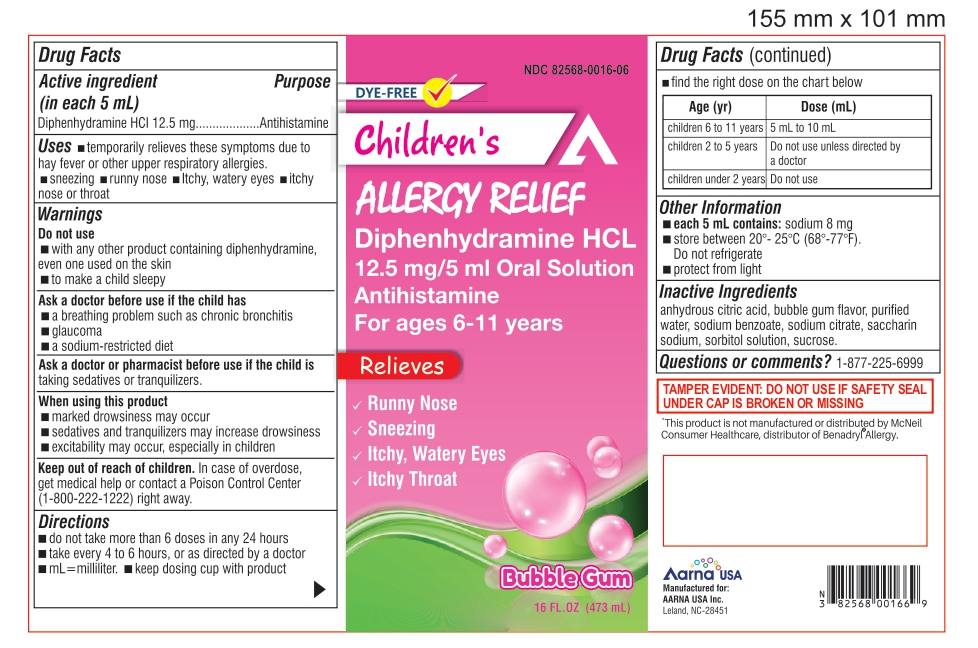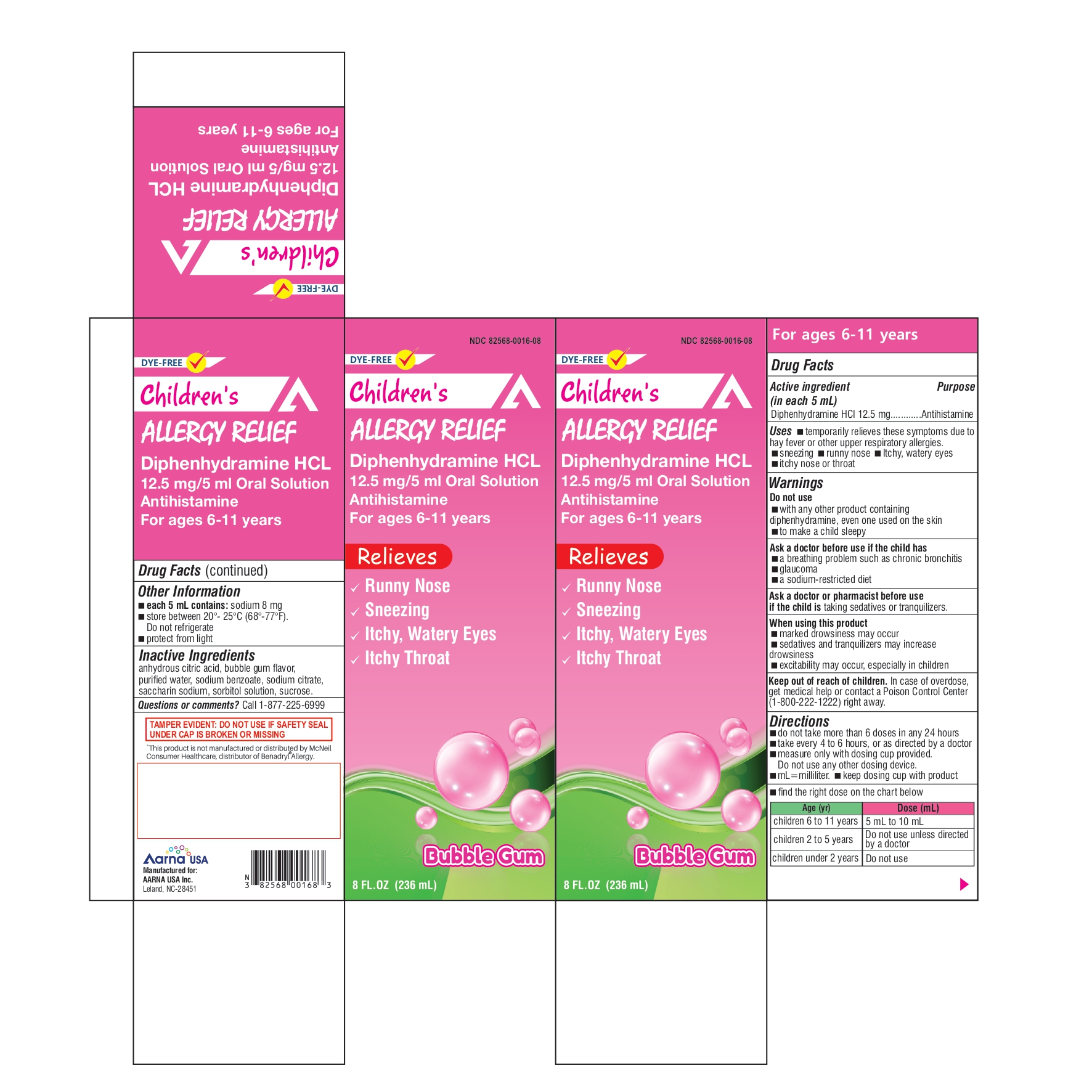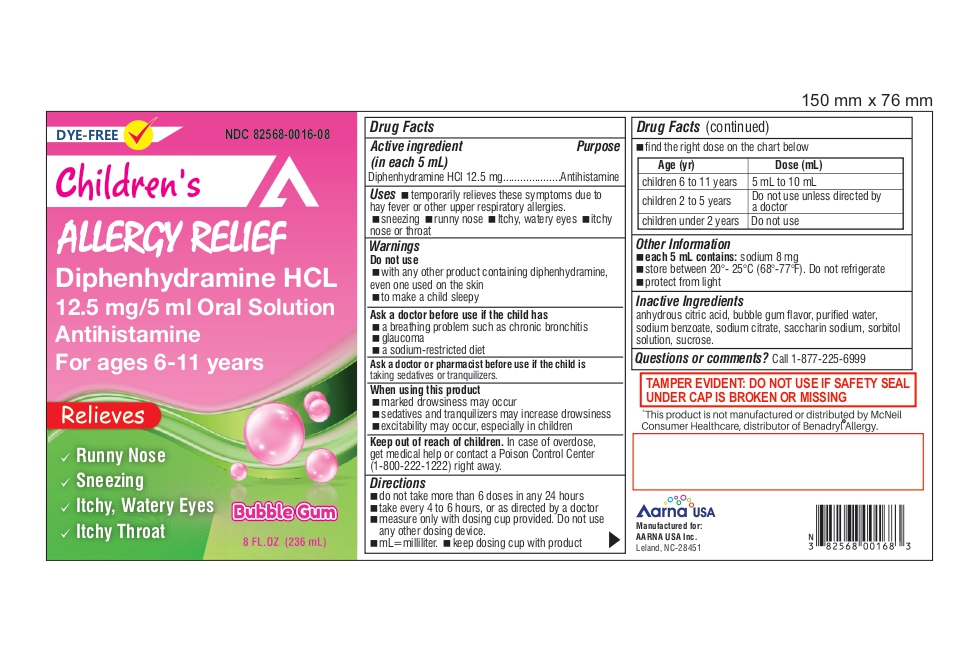 DRUG LABEL: DIPHENHYDRAMINE HCL 12.5 MG PER 5 ML
NDC: 82568-0016 | Form: SOLUTION
Manufacturer: AARNA USA INC.
Category: otc | Type: HUMAN OTC DRUG LABEL
Date: 20250430

ACTIVE INGREDIENTS: DIPHENHYDRAMINE 12.5 mg/5 mL
INACTIVE INGREDIENTS: WATER; SODIUM BENZOATE; SORBITOL SOLUTION; SODIUM SACCHARIN; SODIUM CITRATE; ANHYDROUS CITRIC ACID; SUCROSE

Active ingredient (in each 5 mL)

Diphenhydramine HCl 12.5 mg

Purpose

Antihistamine

Uses

temporarily relieves these symptoms due to hay fever or other upper respiratory allergies:

- sneezing
- runny nose
- itchy, watery eyes
- itchy of the nose or throat

Warnings

Do not use

- with any other product containing diphenhydramine, even one used on skin
- to make a child sleepy

Ask a doctor before use if the child has

- a breathing problem such as chronic bronchitis
- glaucoma
- a sodium restricted diet

Ask a doctor or pharmacist before use if the child is

taking sedatives or tranquilizers.

When using this product

- marked drowsiness may occur
- sedatives and tranquilizers may increase drowsiness
- excitabillty may occur, especially in children

Keep out of reach of children.

In case of overdose, get medical help or contact a Poison Control Center (1-800-222-1222) right away.

Directions

- do not take more than 6 doses in any 24 hours
- take every 4 to 6 hours, or as directed by a doctor
- mL = milliliter
- keep dosing cup with product
- find the right dose on the chart below

Age (yr) | Dose (mL)
children 6 to 11 years | 5 mL to 10 mL
children 2 to 5 years | Do not use unless directed by a doctor
children under 2 years | Do not use

Other Information
each 5 mL contains: sodium 8 mg
Store between 20°- 25°C (68°-77°F). Do not refrigerate
protect from light

Inactive Ingredients
anhydrous citric acid, bubble gum favor, purified water,sodium benzoate, sodium citrate, saccharin sodium, sorbitol solution, sucrose.

Questions or comments?

Please Call 1(877) 225-6999

Manufactured for:

AARNA USA INC

Leland, NC 28451

*This product is not manufactured or distributed by McNeil Consumer Healthcare, distributor of Benadryl® Allergy